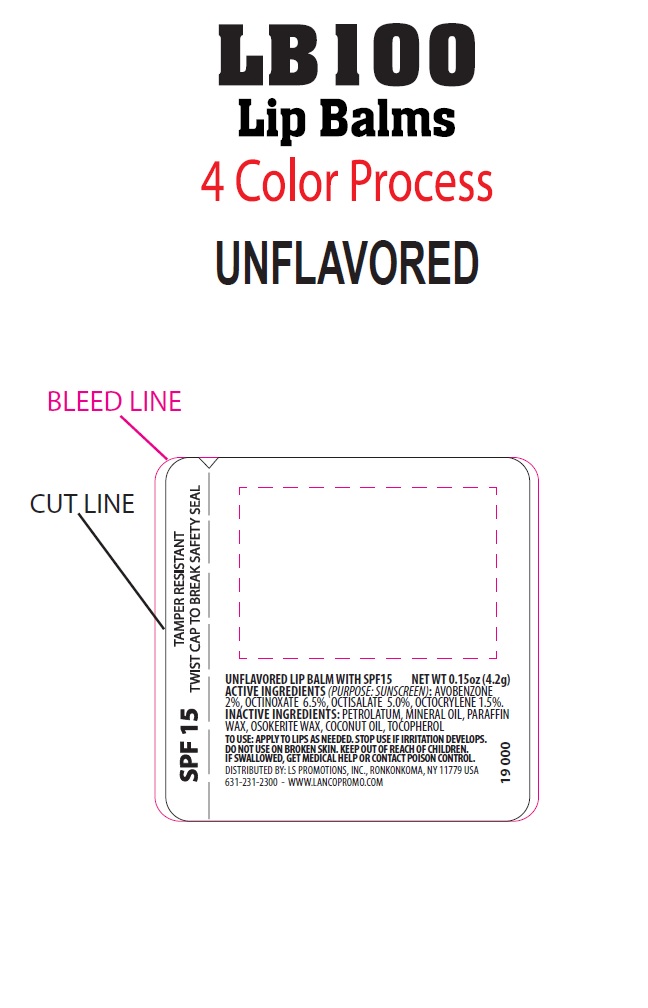 DRUG LABEL: Lip Balm
NDC: 72449-200 | Form: LIPSTICK
Manufacturer: LS Promotions Inc
Category: otc | Type: HUMAN OTC DRUG LABEL
Date: 20210614

ACTIVE INGREDIENTS: OCTISALATE 0.21 g/4.25 g; OCTOCRYLENE 0.06 g/4.25 g; OCTINOXATE 0.28 g/4.25 g; AVOBENZONE 0.09 g/4.25 g
INACTIVE INGREDIENTS: WHITE PETROLATUM; PARAFFIN; CERESIN; MINERAL OIL; COCONUT OIL; TOCOPHEROL

Lip Balm

Drug Fact

Drug Facts

Active Ingredients

Avobenzone 2%

Octinoxate 6.5%

Octisalate 5.0%

Octocrylene 1.5%

Purpose

Sunscreen

Uses

Helps prevent sunburn

Warnings

For external use only

Do not Use on Damaged or Broken Skin

Stop Use and Ask a Doctor

If rash occurs

When using this product

Keep out of eyes. Rinse with water to remove.

Keep out of Reach of Children

If swallowed, get medical help or contact a Poison Control Center

Directions

- Apply liberally 15 minutes before sun exposure
- Reapply at least every 2 hours
- Use a water resistant sunscreen if swimming or sweating
- Children under 6 months of age: Ask a doctor

Sun Protection Measures

Spending time in the sun increases your risk of skin cancer and early skin aging. To decrease this risk, regularly use a sunscreen with a Broad Spectrum SPF value of 15 or higher and other sun protection measures including: Limit time in the sun, especially from 10am to 2pm. Wear long sleeved shirts, pants, hats, and sunglasses.

Inactive Ingredients

Petrolatum, mineral oil, paraffin wax, osokerite wax, coconut oil, tocopherol

Questions or Comments

Call weekdays from 9am to 5pm EST at 631-231-2300

Image of package PDP

Image of label for Lip Balm with SPF15 unflavored

NDC # 72449-200-01